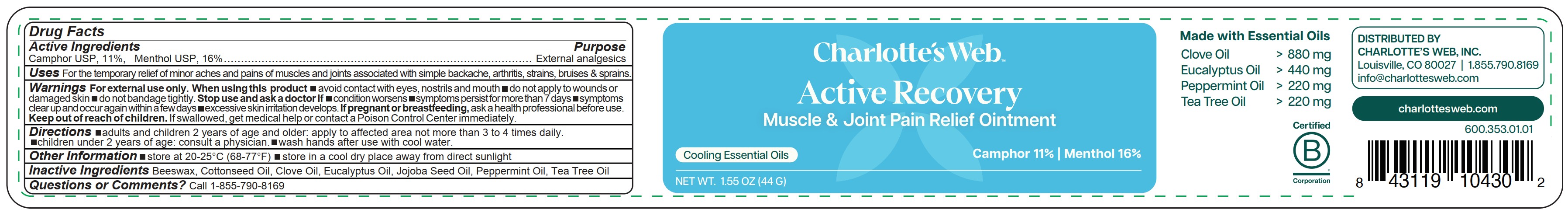 DRUG LABEL: Active Recovery Pain Relief
NDC: 79845-768 | Form: OINTMENT
Manufacturer: Charlotte's Web, Inc.
Category: otc | Type: HUMAN OTC DRUG LABEL
Date: 20250801

ACTIVE INGREDIENTS: MENTHOL 16 g/100 g; CAMPHOR (NATURAL) 11 g/100 g
INACTIVE INGREDIENTS: BEESWAX; COTTONSEED OIL; CLOVE OIL; PEPPERMINT OIL; TEA TREE OIL; JOJOBA OIL; EUCALYPTUS OIL

Active Recovery Pain Relief Ointment

Active ingredients

Camphor USP 11%, Menthol USP 16%

Purpose

Camphor USP 11%, Menthol USP 16%......................External Analgesics

Uses

For the temporary relief of minor aches and pains of muscles and joints associated with simple backache, arthritis, strains, bruises & sprains.

Warnings

For external use only

When using this product

- avoid contact with eyes, nostrils and mouth
- do not apply to wounds or damaged skin
- do not bandage tightly.

Stop use and ask a doctor if

- condition worsens
- symptoms persist for more than 7 days
- symptomsclear up and occur again within a few days
- excessive skin irritation develops.

PREGNANCY OR BREAST FEEDING

If pregnant or breastfeeding,ask a health professional before use

Keep out of reach of children. If swallowed, get medical help or contact a Poison Control Center immediately.

Directions

- adults and children 2 years of age and older: apply to affected area not more than 3 to 4 times daily.
- children under 2 years of age: consult a physician.
- wash hands after use with cool water.

Other information

- store at 20-25°C (68-77°F)
- store in a cool dry place away from direct sunlight

Inactive ingredients

Beeswax, Cottonseed Oil, Clove Oil, Eucalyptus Oil, Jojoba Seed Oil, Peppermint Oil, Tea Tree Oil

Questions or comments?

Call 1-855-790-8169

PACKAGE LABEL

Charlotte's Web

Active Recovery

Muscle & Joint Pain Relief Ointment

Cooling Essential Oils

Camphor 11% | Menthol 16%

NET WT. 1.55 OZ (44 G)